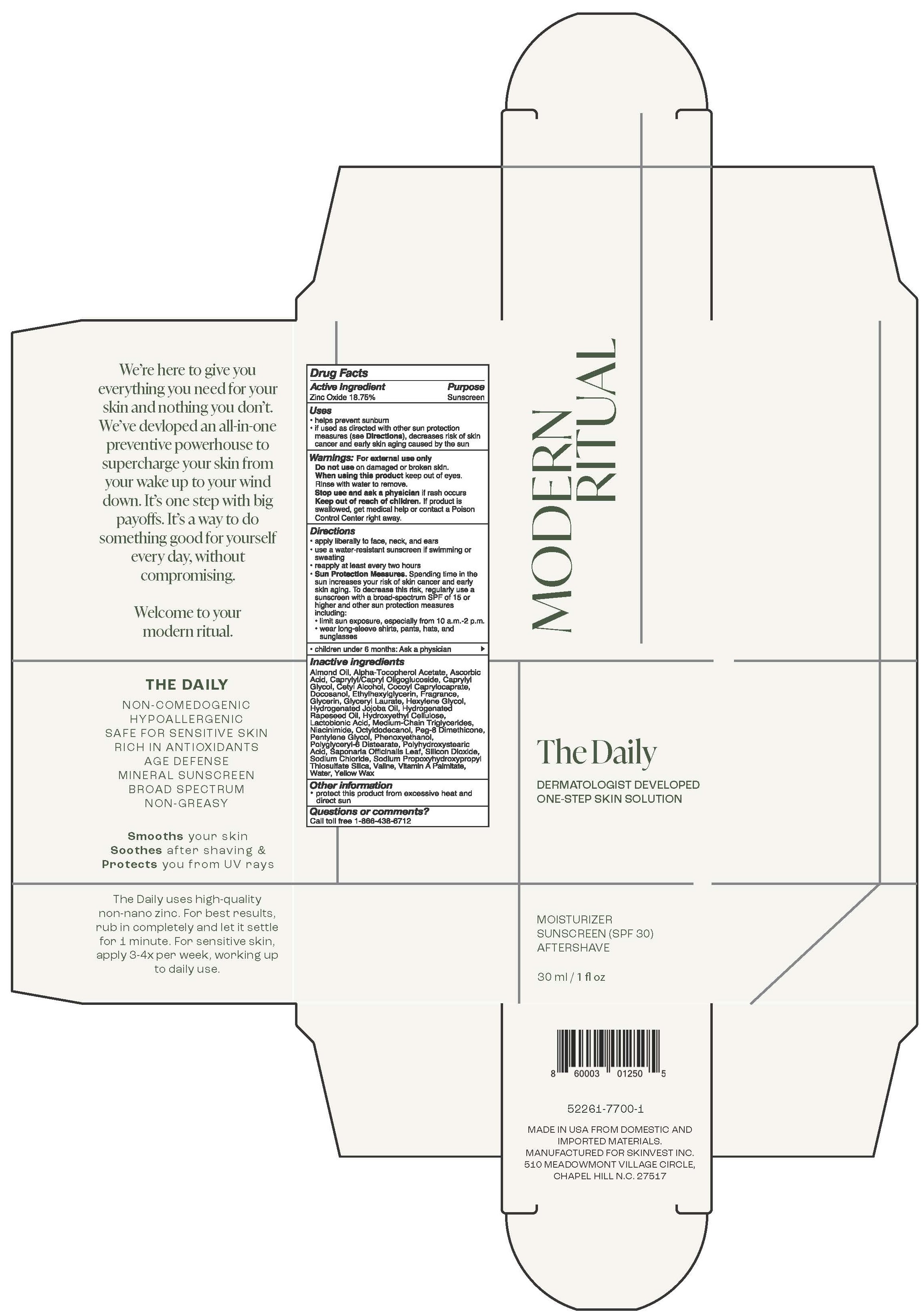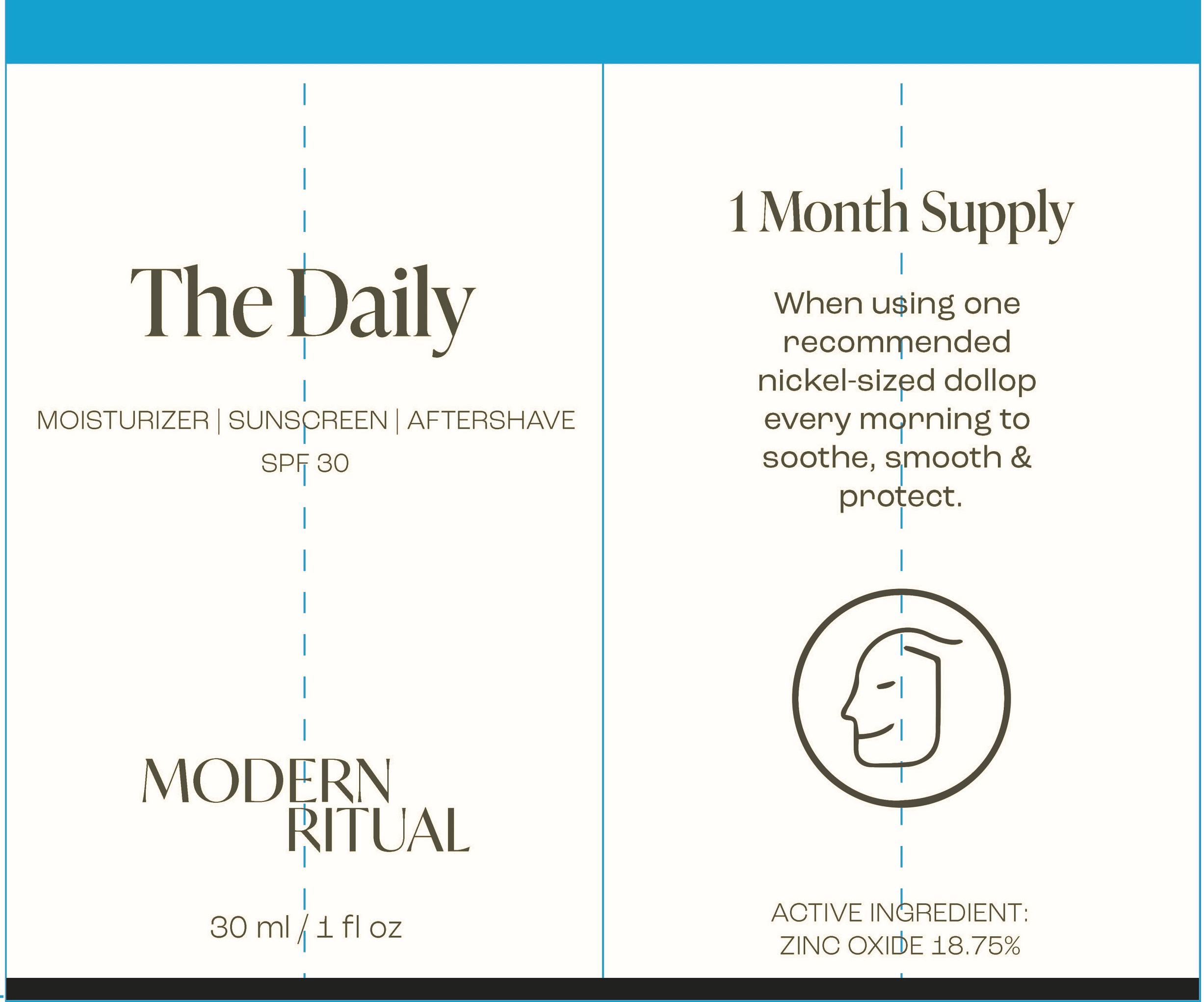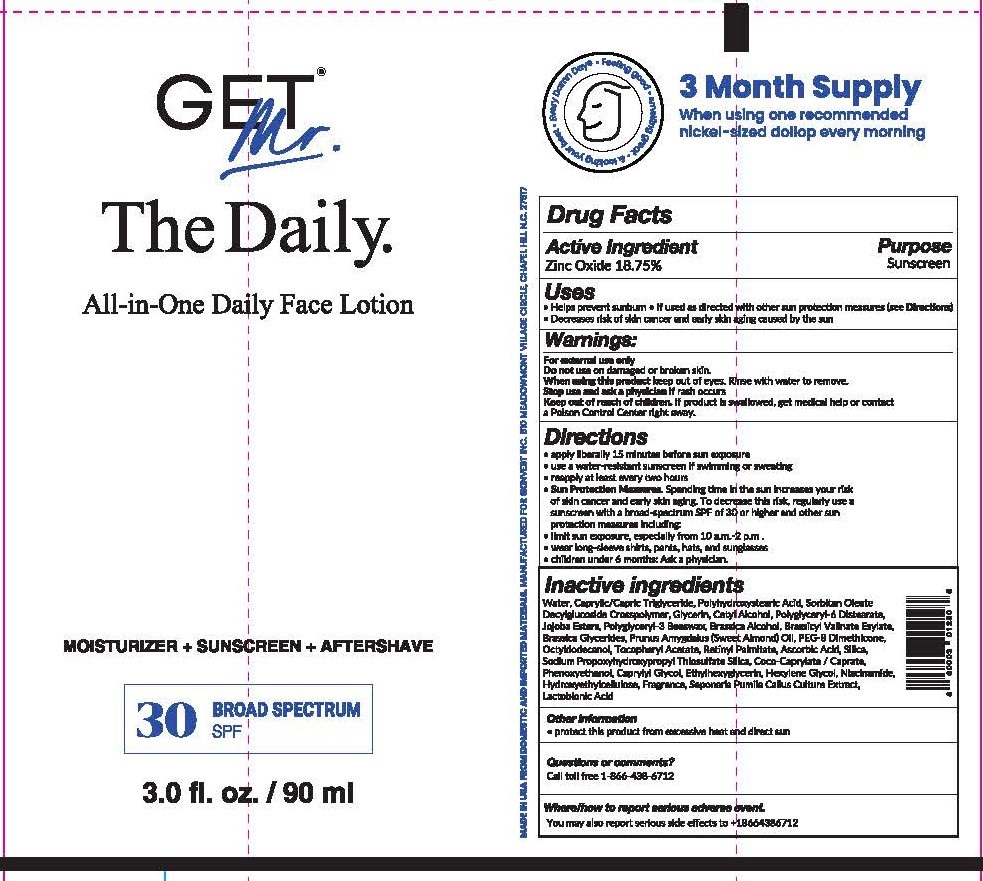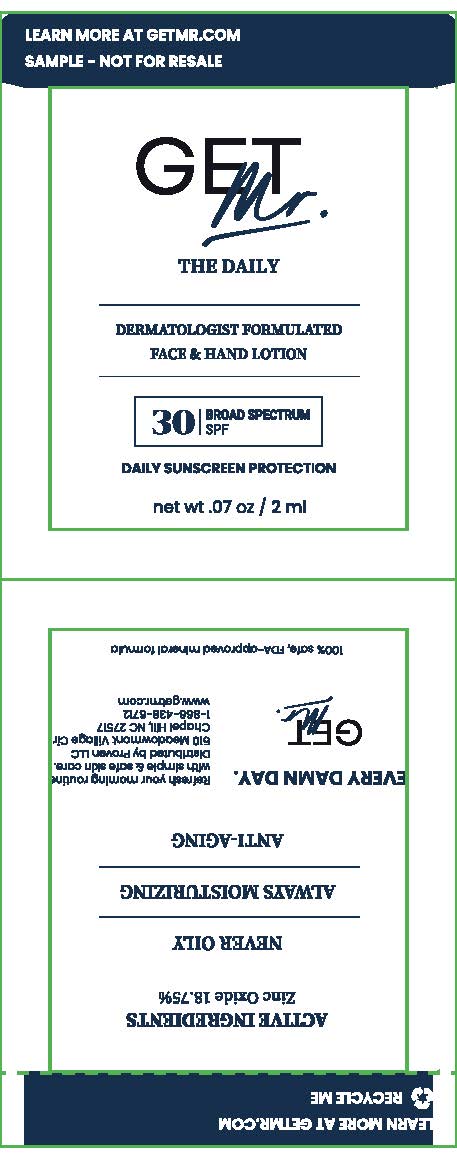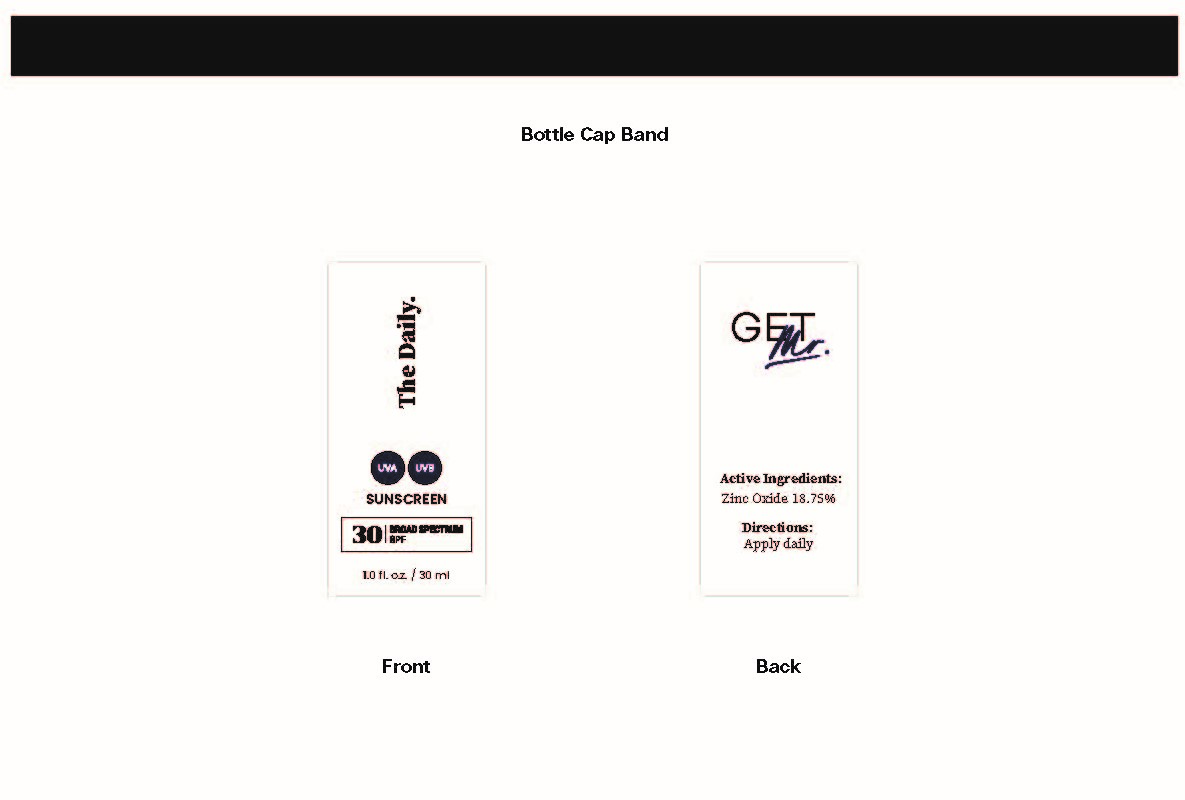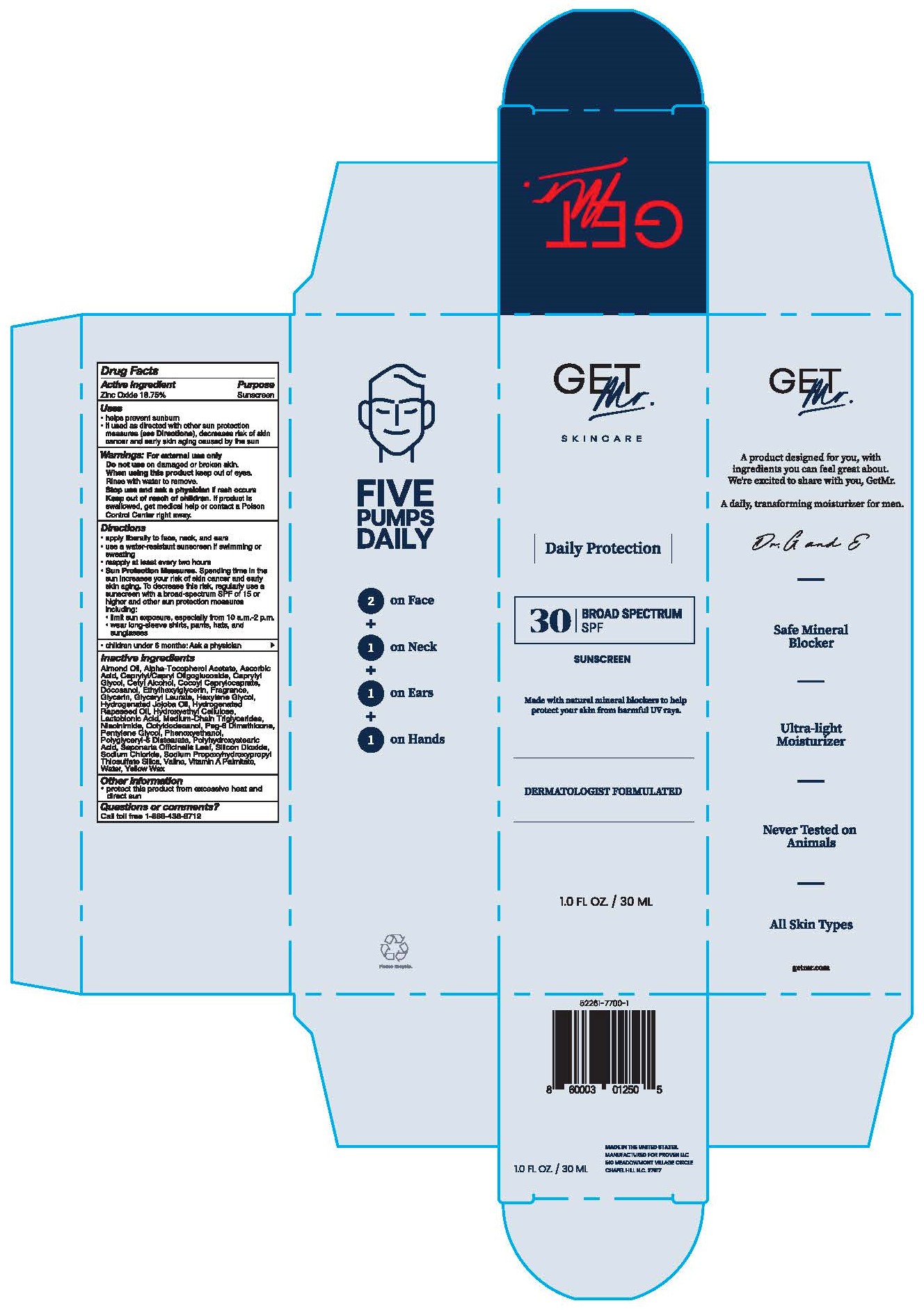 DRUG LABEL: Get Mr Skincare Daily Protection SPF30 Sunscreen
NDC: 52261-7700 | Form: LOTION
Manufacturer: Cosco International, Inc.
Category: otc | Type: HUMAN OTC DRUG LABEL
Date: 20220124

ACTIVE INGREDIENTS: ZINC OXIDE 0.1875 kg/1 kg
INACTIVE INGREDIENTS: WATER; HYDROXYETHYL CELLULOSE, UNSPECIFIED; GLYCERIN; NIACINAMIDE; GLYCERYL LAURATE; MEDIUM-CHAIN TRIGLYCERIDES; POLYHYDROXYSTEARIC ACID (2300 MW); ALMOND OIL; COCOYL CAPRYLOCAPRATE; PHENOXYETHANOL; CAPRYLYL GLYCOL; ETHYLHEXYLGLYCERIN; HEXYLENE GLYCOL; PEG-8 DIMETHICONE; OCTYLDODECANOL; .ALPHA.-TOCOPHEROL ACETATE; VITAMIN A PALMITATE; ASCORBIC ACID; SILICON DIOXIDE; SODIUM PROPOXYHYDROXYPROPYL THIOSULFATE SILICA; POLYGLYCERYL-6 DISTEARATE; HYDROGENATED JOJOBA OIL, RANDOMIZED; YELLOW WAX; CETYL ALCOHOL; CAPRYLYL/CAPRYL OLIGOGLUCOSIDE; PENTYLENE GLYCOL; SODIUM CHLORIDE; HYDROGENATED RAPESEED OIL; VALINE; DOCOSANOL; SAPONARIA OFFICINALIS LEAF; LACTOBIONIC ACID

Drug Facts

Drug Facts

Active Ingredient...........................Purpose

Zinc Oxide 18.75%..........................Sunscreen

Uses

- helps prevent sunburn
- if used as directed with other sun protection measures (see Directions), decreases the risk of skin cancer and early aging caused by the sun

Warnings

- For external use only

- Do not use on damaged or borken skin

- When using this product keep out of eyes. Rinse with water to remove

- Stop use and ask a physician if rash occurs

- Keep out of reach of children. If product is swallowed, get medical help or contact a Poison Control Center right away.

Directions

- apply liberally to face, neck, and ears
- use a water-resistant sunscreen if swimming or sweating
- reapply at least every two hours
- Sun Protection Measures. Spending time in the sun increases your risk of skin cancer and early skin aging. To decrease this risk, regularly use a sunscreen with a broad-spectrum SPF of 15 or higher and other sun protection measures including:
- limit time in the sun, especially from 10 a.m.-2 p.m.
- wear long-sleeve shirts, pants, hats, and sunglasses
- children under 6 months: Ask a physician

Inactivve Ingredients

ALMOND OIL, ALPHA-TOCOPHEROL ACETATE, ASCORBIC ACID, CAPRYLYL/CAPRYL OLIGOGLUCOSIDE, CAPRYLYL GLYCOL, CETYL ALCOHOL, COCOYL CAPRYLOCAPRATE, DOCOSANOL, ETHYLHEXYLGLYCERIN, FRAGRANCE, GLYCERIN, GLYCERYL LAURATE, HEXYLENE GLYCOL, HYDROGENATED JOJOBA OIL, HYDROGENATED RAPESEED OIL, HYDROXYETHYL CELLULOSE, LACTOBIONIC ACID, MEDIUM-CHAIN TRIGLYCERIDES, NIACINAMIDE, OCTYLDODECANOL, PEG-8 DIMETHICONE, PENTYLENE GLYCOL, PHENOXYETHANOL, POLYGLYCERYL-6 DISTEARATE, POLYHYDROXYSTEARIC ACID, SAPONARIA OFFICINALIS LEAF, SILICON DIOXIDE, SODIUM CHLORIDE, SODIUM PROPOXYHYDROXYPROPYL THIOSULFATE SILICA, VALINE, VITAMIN A PALMITATE, WATER, YELLOW WAX

Other Information

• Protect this product from excessive heat and direct sun

Questions or comments?

Call toll free 1-866-438-6712